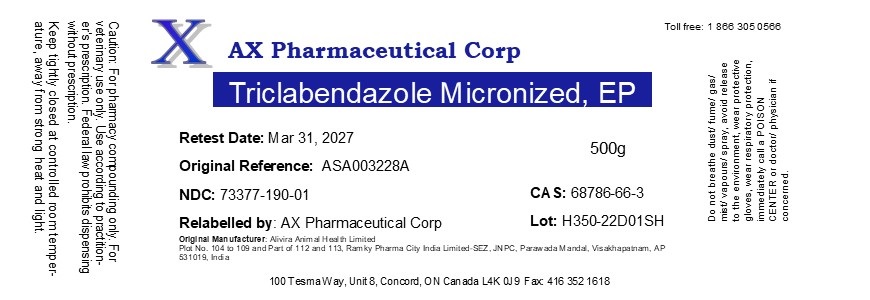 DRUG LABEL: Triclabendazole Micronized
NDC: 73377-190 | Form: POWDER
Manufacturer: AX Pharmaceutical Corp
Category: other | Type: BULK INGREDIENT - ANIMAL DRUG
Date: 20220915

ACTIVE INGREDIENTS: TRICLABENDAZOLE 1 g/1 g

Triclabendazole Micronized